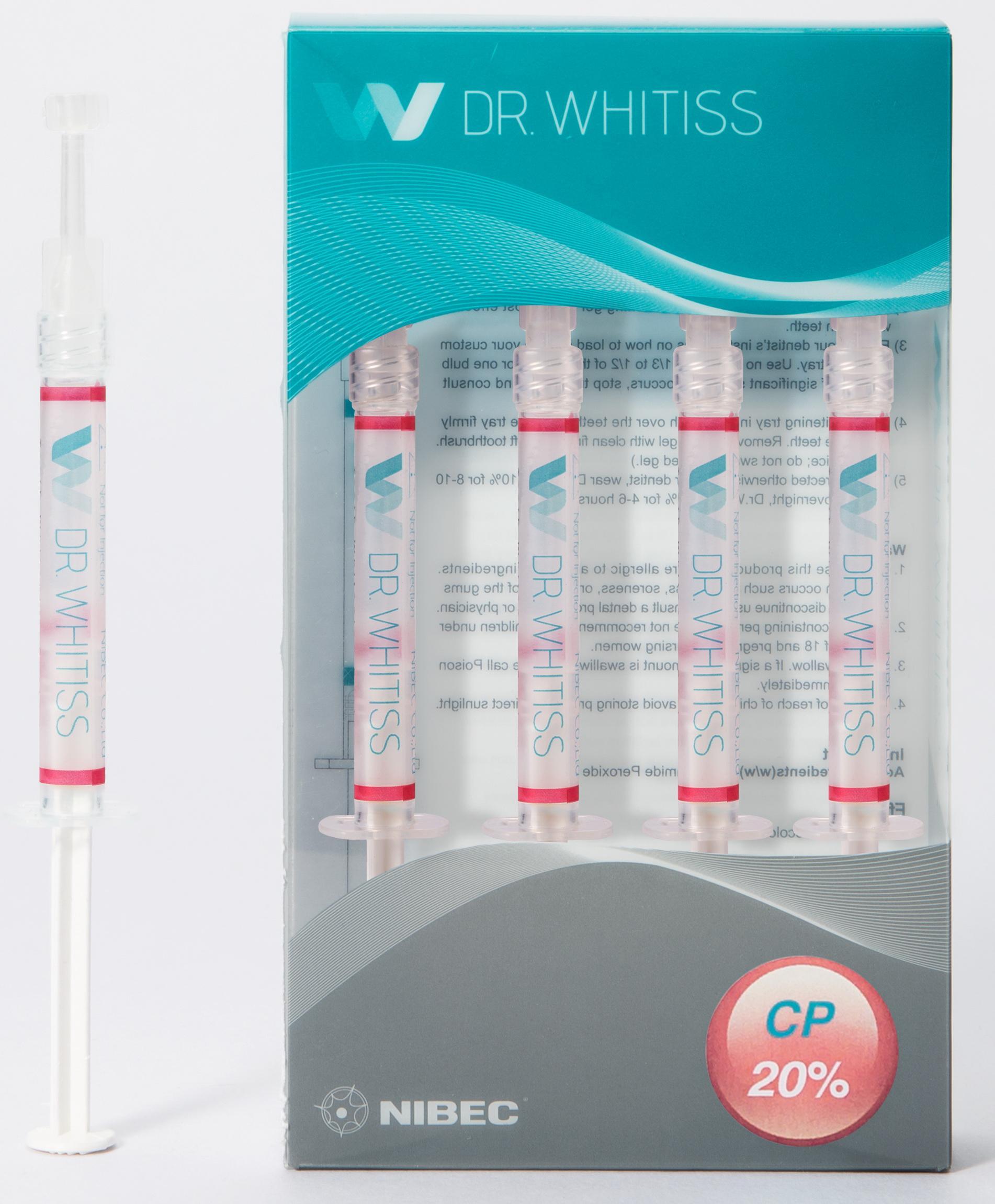 DRUG LABEL: Dr.Whitiss 20%
NDC: 47649-1201 | Form: GEL, DENTIFRICE
Manufacturer: Nibec Co., Ltd
Category: otc | Type: HUMAN OTC DRUG LABEL
Date: 20181226

ACTIVE INGREDIENTS: CARBAMIDE PEROXIDE 20 g/100 g
INACTIVE INGREDIENTS: POVIDONE K90; GLYCERIN; WATER; POTASSIUM NITRATE

Drug Facts

ACTIVE INGREDIENT

carbamide peroxide

INACTIVE INGREDIENT

pyrrolidone (k=90), hydroxyethyl cellulose, glycerin, purified water, monobasic potassium phosphate, sodiu hydroxide, l-menthol, potassium nitrate, anhydrous ethanol

PURPOSE

whitening of discolored teeth

keep out of reach of the children

INDICATIONS AND USAGE

1. Gingival and general oral heath should be confirmed before treatment.
2. Brush your teeth before treatment.
3. Follow your dentist’s instructions on how to load gel into your custom whitening tray. Use no more than 1/3 to 1/2 of the syringe per tray.
4. Insert whitening tray in the mouth over the teeth. Seat the tray firmly agains the teeth. Remove excess gel with clean finger or soft toothbrush.(Rinse twice; do not swallow rinsed gel.)
5. Unless directed otherwise by your dentist, wear Dr.Whitiss 10% for 8-10 hours or overnight, Dr.Whitiss 15% for 4-6 hours, Dr.Whitiss20% for 2-4 hours, and Dr.Whitiss 35% for 30 minutes.
6. If significant sensitivity occurs, stop treatment and consult dentist.

WARNINGS

1) do not use on patient with sensitive to carbamide peroxide
2) do not use on patient with oral infection
3) no to be used by pregnant or lactating women or children under 18 years old
4) to be used under the supervision of a dentist
5) do not swallow this medication

DOSAGE AND ADMINISTRATION

for dental use only